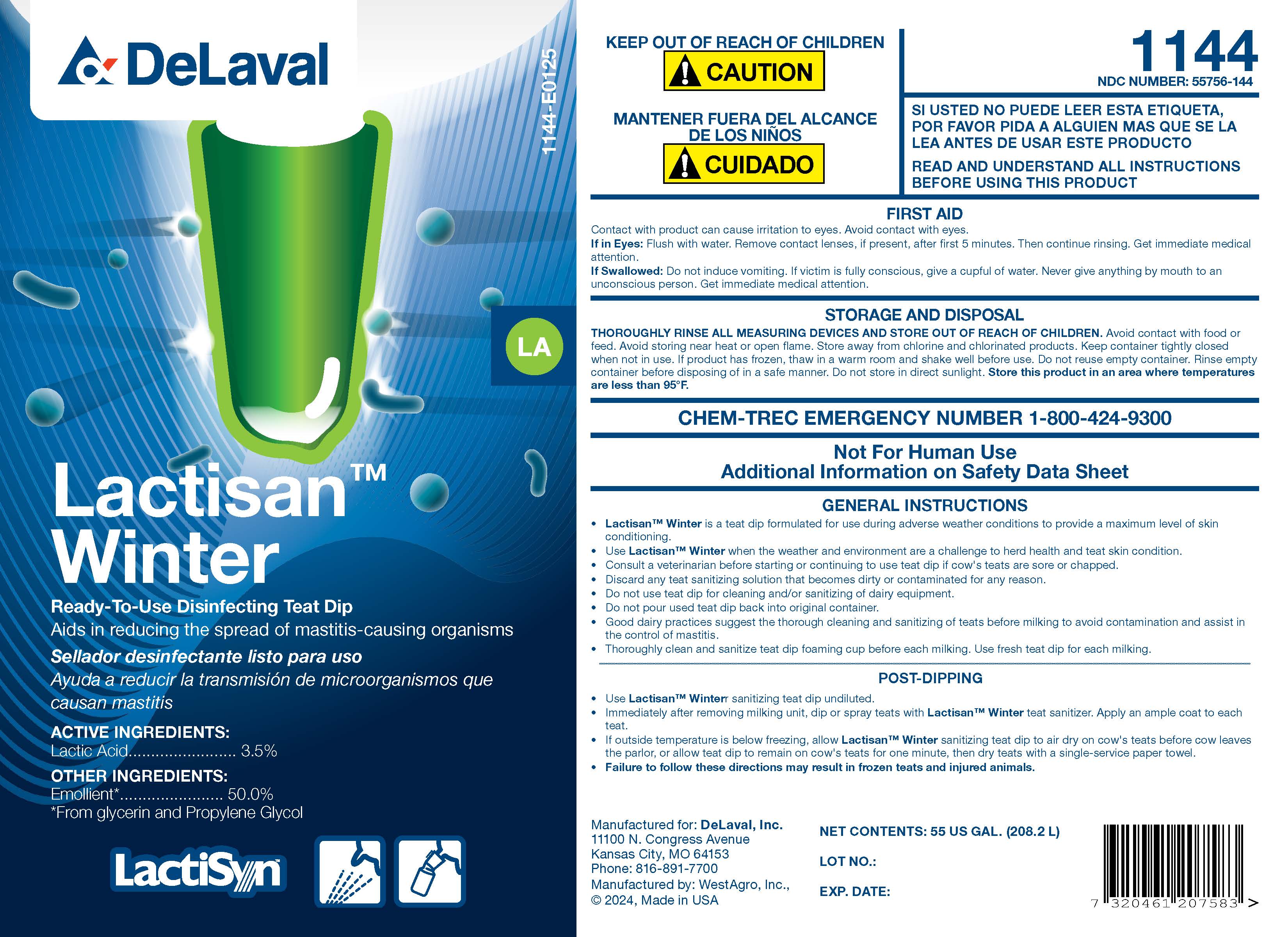 DRUG LABEL: Lactisan Winter
NDC: 55756-144 | Form: SOLUTION
Manufacturer: DeLaval
Category: animal | Type: OTC ANIMAL DRUG LABEL
Date: 20250225

ACTIVE INGREDIENTS: LACTIC ACID, L- 42.3 g/1 L
INACTIVE INGREDIENTS: WATER; GLYCERIN; PROPYLENE GLYCOL; SALICYLIC ACID; ALLANTOIN; BENZYL ALCOHOL; POLOXAMER 338; DOCUSATE SODIUM; POLYSORBATE 80; SODIUM HYDROXIDE; FD&C YELLOW NO. 5; FD&C BLUE NO. 1

DeLaval Lactisan Winter

INDICATIONS AND USAGE

Ready-To-Use Disinfecting Teat Dip

Aids in reducing the spread of mastitis-causing organisms

ACTIVE INGREDIENTS:

Lactic Acid ................................ 3.5%

OTHER INGREDIENTS:

Emollient* .......................... 50.0%

*From glycerin and Propylene Glycol

KEEP OUT OF REACH OF CHILDREN

! CAUTION

MANTENER FUERA DEL ALCANCE DE LOS NINOS

!CUIDADO

1144

NDC 55756-144

SI USTED NO PUEDE LEER ESTA ETIQUETA, POR FAVOR PIDA A ALGUIEN MAS QUE SE LA LEA ANTES DE USAR ESTE PRODUCTO

READ AND UNDERSTAND ALL INSTRUCTIONS BEFORE USING THIS PRODUCT

FIRST AID

Contact with product can cause irritation to eyes. Avoid contact with eyes.

If in Eyes: Flush with water. Remove contact lenses, if present, after first 5 minutes. Then continue rinsing. Get immediate medical attention.

If Swallowed: Do not induce vomiting. If victim is fully conscious, give a cupful of water. Never give anything by mouth to an unconscious person. Get immediate medical attention.

STORAGE AND DISPOSAL

THOROUGHLY RINSE ALL MEASURING DEVICES AND STORE OUT OF REACH OF CHILDREN. Avoid contact with food or feed. Avoid storing near heat or open flame. Store away from chlorine and chlorinated products. Keep container tightly closed when not in use. If product has frozen, thaw in a warm room and shake well before use. Do not reuse empty container. Rinse empty container before disposing of in a safe manner. Do not store in direct sunlight. Store this product in an area where temperatures are less than 95 F.

CHEM-TREC EMERGENCY NUMBER 1-800-424-9300

Not for Human Use

Additional Information on Safety Data Sheet

GENERAL INSTRUCTIONS

- Lactisan™ Winter is a teat dip formulated for use during adverse weather conditions to provide a maximum level of skin conditioning.
- Use Lactisan™ Winter when the weather and environment are a challenge to herd health and teat skin condition.
- Consult a veterinarian before starting or continuing to use teat dip if cow's teats are sore or chapped.
- Discard any teat sanitizing solution that becomes dirty or contaminated for any reason.
- Do not use teat dip for cleaning and/or sanitizing of dairy equipment.
- Do not pour used teat dip back into original container.
- Good dairy practices suggest the thorough cleaning and sanitizing of teats before milking to avoid contamination and assist in the control of mastitis.
- Thoroughly clean and sanitize teat dip foaming cup before each milking. Use fresh teat dip for each milking.

POST-DIPPING

- Use Lactisan™ Winter sanitizing teat dip undiluted.
- Immediately after removing milking unit, dip or spray teats with Lactisan™ Winter teat sanitizer. Apply an ample coat to each teat.
- If outside temperature is below freezing, allow Lactisan™ Winter sanitizing teat dip to air dry on cow's teats before cow leaves the parlor, or allow teat dip to remain on cow's teats for one minute, then dry teats with a single-service paper towel.
- Failure to follow these directions may result in frozen teats and injured animals.

Manufactured for: DeLaval, Inc.
11100 N. Congress Avenue
Kansas City, MO 64153
Phone: 816-891-7700
Manufactured by: WestAgro, Inc.,
©2024, Made in USA

NET CONTENTS: US GAL. (L)

LOT NO.:

EXP. DATE:

PACKAGE LABEL

Add image transcription here...